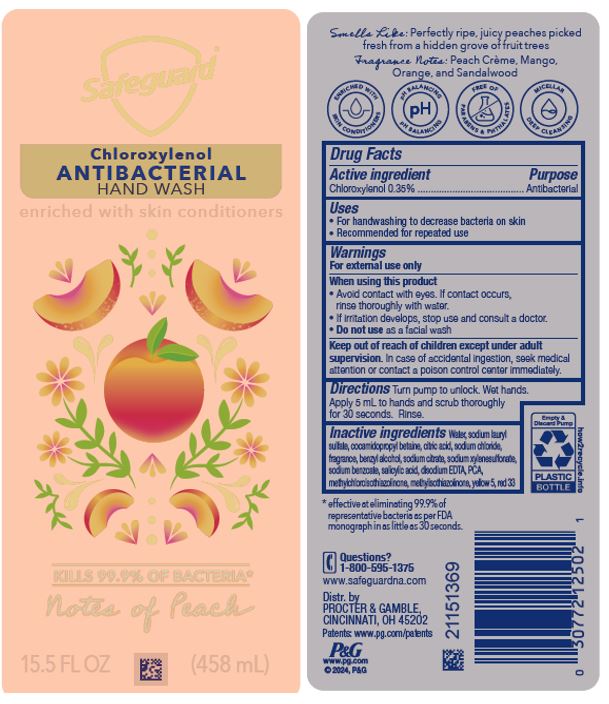 DRUG LABEL: Safeguard Antibacterial Hand Wash
NDC: 84126-007 | Form: SOAP
Manufacturer: The Procter & Gamble Manufacturing Company
Category: otc | Type: HUMAN OTC DRUG LABEL
Date: 20251231

ACTIVE INGREDIENTS: CHLOROXYLENOL 0.35 g/100 mL
INACTIVE INGREDIENTS: METHYLCHLOROISOTHIAZOLINONE; SODIUM LAURYL SULFATE; COCAMIDOPROPYL BETAINE; BENZYL ALCOHOL; EDETATE DISODIUM; WATER; D&C RED NO. 33; FD&C YELLOW NO. 5; SODIUM CITRATE; SODIUM XYLENESULFONATE; SODIUM CHLORIDE; SODIUM BENZOATE; SALICYLIC ACID; PIDOLIC ACID; METHYLISOTHIAZOLINONE; CITRIC ACID MONOHYDRATE

Safeguard® AntiBacterial Hand Wash Notes of Peach

Drug Facts

Active Ingredient

Chloroxylenol 0.35%

Purpose

Antibacterial

Uses

- For handwashing to decrease bacteria on the skin
- Recommended for repeated use

Warnings

For external use only

When using this product

- Avoid contact with eyes. If contact occurs, rinse thoroughly with water.
- If irritation develops, stop use and consult a doctor.
- Do not use as a facial wash

Keep out of reach of children except under adult supervision

In case of accidental ingestion, seek medical attention or contact a poison control center immediately.

Directions

Turn pump to unlock.Wet hands. Apply 5 mL to hands and scrub thoroughly for 30 seconds. Rinse.

Inactive ingredients

Water, sodium lauryl sulfate, cocamidopropyl betaine, citric acid, sodium chloride, fragrance, benzyl alcohol, sodium citrate, sodium xylenesulfonate, sodium benzoate, salicylic acid, disodium EDTA, PCA, methylchloroisothiazolinone, methylisothiazolinone, yellow5, red33

Questions?

1-800-595-1375

www.safeguardna.com

Distr. by

Procter & Gamble,

Cincinnati, OH 45202

PRINCIPAL DISPLAY PANEL - 458 mL Label

Safeguard®

Chloroxylenol
Antibacterial

Hand Wash Kills 99.9% of bacteria

Notes of Peach

15.5 FL OZ 458 mL